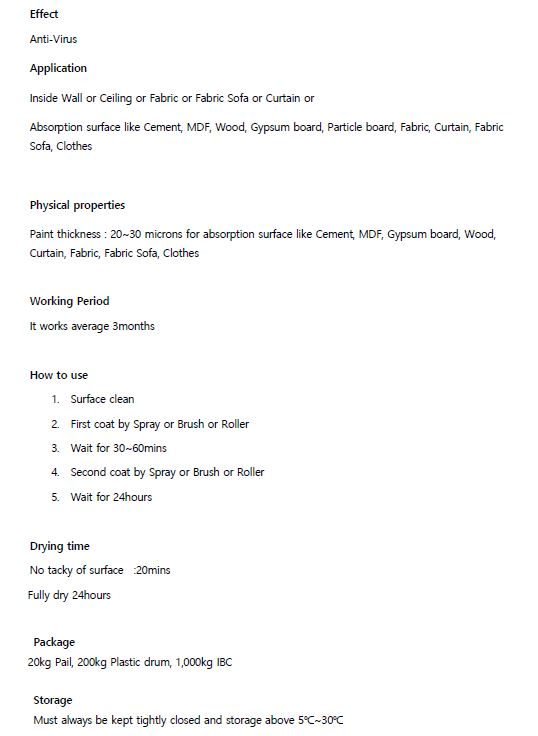 DRUG LABEL: NWK A-FV
NDC: 82081-0003 | Form: LIQUID
Manufacturer: Nae Woi Korea Ltd
Category: otc | Type: HUMAN OTC DRUG LABEL
Date: 20230525

ACTIVE INGREDIENTS: CINNAMON OIL 100 g/100 mL
INACTIVE INGREDIENTS: WATER

ACTIVE INGREDIENT

cinnamon oil 100%

INACTIVE INGREDIENT

n/a

PURPOSE

Sterilizing agent

WARNINGS

■ if following abnormal symptoms persist, discontinue use

Irritation around the eyes, ears, mucous membranes, including the mouth, under the skin irritation and rashes

■ Stop immediately and consult a doctor if you experience

1) Hypersensitivity symptoms such as erythema, itching and dermatitis.

2) Skin Irritation

3) Following Instructions when using medication

(1) For external use only (Do not use internally)

(2) Avoid getting into the eyes (if contact occurs, wash well with clean water)

■ Be careful not to inhale or use excessively for a long time (ingesting ethanol repeatedly causes irritation to mucous membranes and headaches or other symptoms may appear. When used repeatedly in the same area, skin irritation may occur.

■ Do not use the product for a long time in the same area as swelling, inflammation or sickness may occur due to absorption through the skin.

It is not recommended to use this one areas that have been medically treated with a cast or bandage.

■ Do not use in combination with soap or antibacterial cleansing agents.

Keep Out of Reach of Children.

INDICATIONS AND USAGE

apply where needed

DOSAGE AND ADMINISTRATION

for external use only